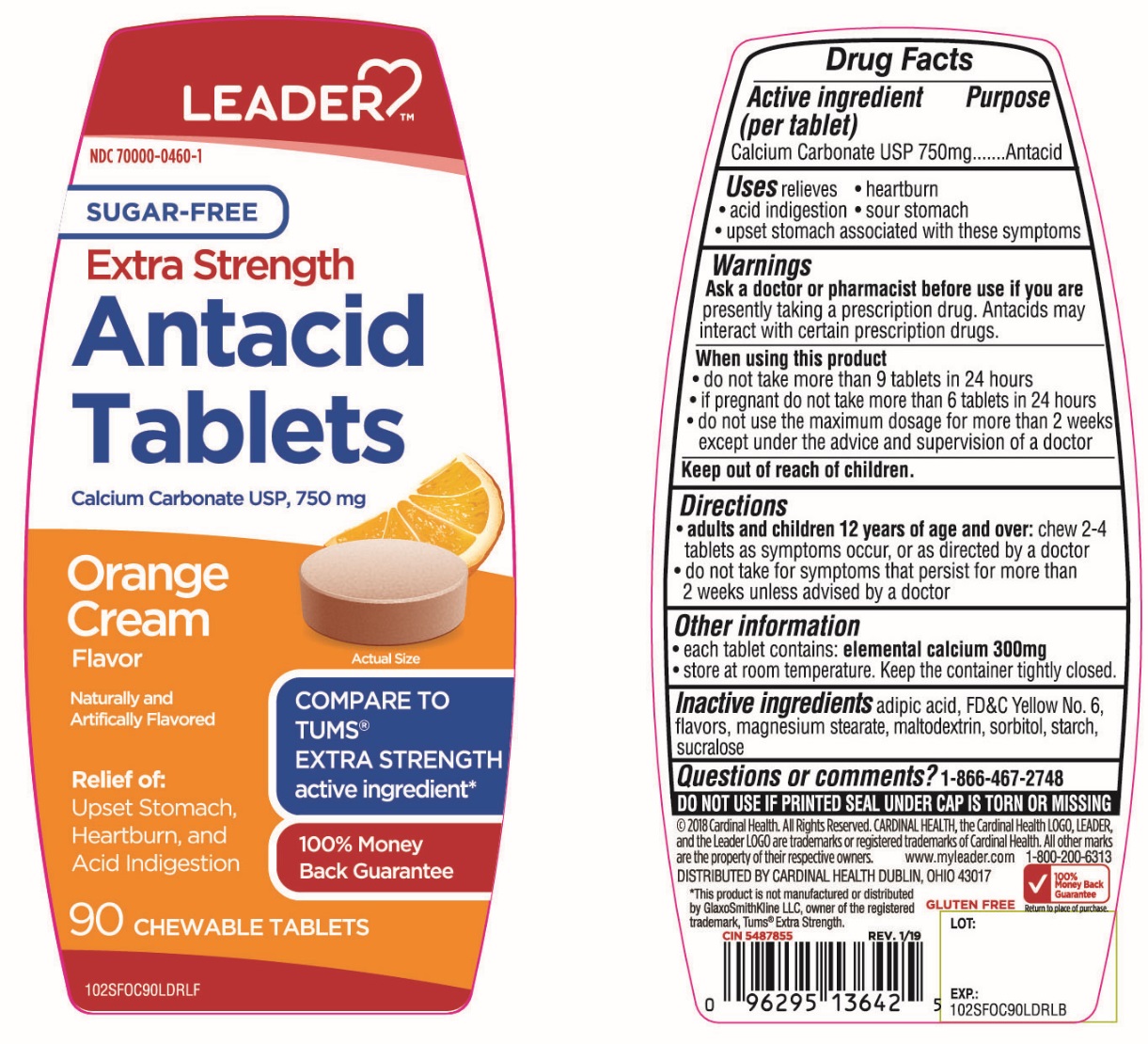 DRUG LABEL: Leader Extra Strength Sugar Free Antacid
NDC: 70000-0460 | Form: TABLET, CHEWABLE
Manufacturer: Cardinal Health
Category: otc | Type: HUMAN OTC DRUG LABEL
Date: 20251014

ACTIVE INGREDIENTS: CALCIUM CARBONATE 750 mg/1 1
INACTIVE INGREDIENTS: ADIPIC ACID; FD&C YELLOW NO. 6; MAGNESIUM STEARATE; MALTODEXTRIN; SORBITOL; STARCH, CORN; SUCRALOSE

Leader Health Extra Strength SUGAR FREE Antacid Tablets Calcium Carbonate 750 mg

Active ingredient (per tablet)

Calcium Carbonate USP 750 mg

Purpose

Antacid

Uses

relieves

• heartburn

• acid indigestion

• sour stomach

• upset stomach associated with these symptoms

Warnings

Ask a doctor or pharmacist before use if you arepresently taking a prescription drug. Antacids may interact with certain prescription drugs.

When using this product

- do not take more than 9 tablets in 24 hours
- If pregnant do not take more than 6 tablets in 24 hours
- do not use the maximum dosage for more than 2 weeks except under the advice and supervision of a doctor

Directions

- adults and children 12 years of age and over:chew 2-4 tablets as symptoms occur ,or as directed by a doctor
- do not take for symptoms that persist for more than 2 weeks unless advised by a doctor

Other Information

• each tablet contains: elemental calcium 300 mg

• store at room temperature. Keep the container tightly closed.

Inactive ingredients

adipic acid, FD&C Yellow No. 6, flavors, magnesium stearate, maltodextrin, sorbitol, starch, sucralose.

Questions or comments?

1-866-467-2748

SAFETY SEALED: DO NOT USE IF PRINTED SEAL UNDER CAP IS TORN OR MISSING

Package/Label Principal Display Panel

NDC 70000-0460-1

LEADER™

COMPARE TO TUMS® EXTRA STRENGTH active ingredient *

100% Money Back Guarantee

SUGAR-FREE

EXTRA STRENGTH

Antacid

Tablets

Calcium Carbonate USP 750 mg

- Orange Cream Flavor
- Naturally and Artificially Flavored
- GLUTEN FREE
- Relief of:
- Upset Stomach, Heartburn, and Acid Indigestion

90 CHEWABLE TABLETS

© 2018 Cardinal Health.

All Rights Reserved.

CARDINAL HEALTH, the Cardinal Health LOGO, LEADER and the Leader LOGO are the trademarks or registered trademarks of Cardinal Health.

All other marks are the property of their respective owners.

www.myleader.com

1-800-200-6313

DISTRIBUTED BY: CARDINAL HEALTH

DUBLIN, OHIO 43017

*This product is not manufactured or distributed by GlaxoSmithKline LLC, owner of the registered trademark, TUMS®Extra Strength.